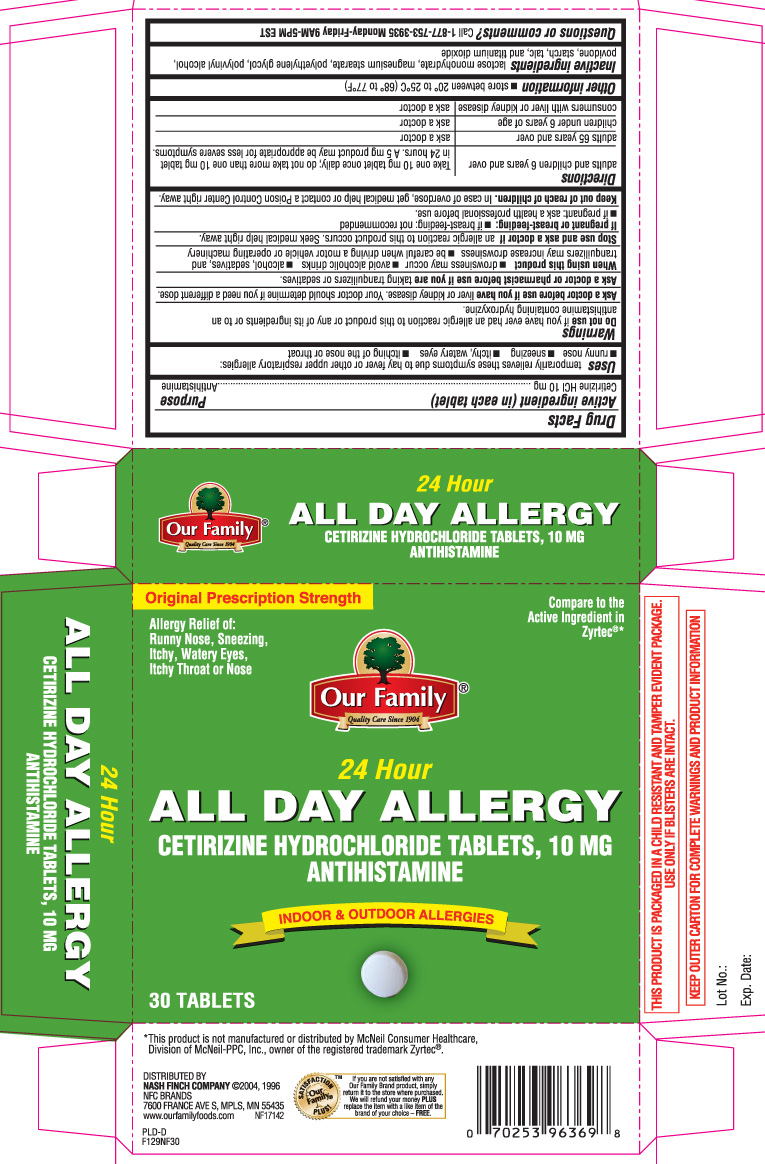 DRUG LABEL: All Day Allergy Relief
NDC: 70253-129 | Form: TABLET
Manufacturer: OUR FAMILY (NASH FINCH COMPANY)
Category: otc | Type: HUMAN OTC DRUG LABEL
Date: 20130304

ACTIVE INGREDIENTS: CETIRIZINE HYDROCHLORIDE 10 mg/1 1
INACTIVE INGREDIENTS: LACTOSE MONOHYDRATE; MAGNESIUM STEARATE; POLYETHYLENE GLYCOLS; POVIDONES; STARCH, CORN; TALC; TITANIUM DIOXIDE; POLYVINYL ALCOHOL

DRUG FACTS

Active ingredient (in each tablet)

Cetirizine HCl 10 mg

Purpose

Antihistamine

Uses

temporarily relieves these symptoms due to hay fever or other upper respiratory allergies:

- runny nose
- sneezing
- itchy, watery eyes
- itching of the nose or throat

Warnings

Do not use

if you have ever had an allergic reaction to this product or any of its ingredients or to an antihistamine containing hydroxyzine.

Ask a doctor before use if you have

liver or kidney disease. Your doctor should determine if you need a different dose.

Ask a doctor or pharmacist before use if you are

taking tranquilizers or sedatives.

When using this product

- drowsiness may occur
- avoid alcoholic drinks
- alcohol, sedatives, and tranquilizers may increase drowsiness
- be careful when driving a motor vehicle or operating machinery

Stop use and ask a doctor if

an allergic reaction to this product occurs. Seek medical help right away.

If pregnant or breast-feeding:

- if breast-feeding: not recommended
- if pregnant: ask a health professional before use

Keep out of reach of children.

In case of overdose, get medical help or contact a Poison Control Center right away.

Directions

adults and children 6 years and over | Take one 10 mg tablet once daily; do not take more than one 10 mg tablet in 24 hours. A 5 mg product may be appropriate for less severe symptoms.
adults 65 years and over | ask a doctor
children under 6 years of age | ask a doctor
consumers with liver or kidney disease | ask a doctor

Other information

- store between 20° to 25°C (68° to 77°F)

Inactive ingredients

lactose monohydrate, magnesium stearate, polyethylene glycol, polyvinyl alcohol, povidone, starch, talc, and titanium dioxide

Questions or comments?

Call 1-877-753-3935 Monday-Friday 9AM-5PM EST

Principal Display Panel

Original Prescription Strength

Allergy Relief of: Runny Nose, Sneezing, Itchy, Watery Eyes, Itchy Throat or Nose

Compare to the Active Ingredient in Zyrtec®*

24 Hour

ALL DAY ALLERGY

CETIRIZINE HYDROCHLORIDE TABLETS, 10 MG

ANTIHISTAMINE

INDOOR & OUTDOOR ALLERGIES

TABLETS

*This product is not manufactured or distributed by McNeil Consumer Healthcare, Division of McNeil-PPC, Inc., owner of the registered trademark Zyrtec®.

DISTRIBUTED BY

NASH FINCH COMPANY ©2004, 1996

NFC BRANDS

7600 FRANCE AVE S, MPLS, MN 55435

THIS PRODUCT IS PACKAGED IN A CHILD RESISTANT AND TAMPER EVIDENT PACKAGE. USE ONLY IF BLISTERS ARE INTACT.

KEEP OUTER CARTON FOR COMPLETE WARNINGS AND PRODUCT INFORMATION

Product Label

Our Family All Day Allergy Tablets